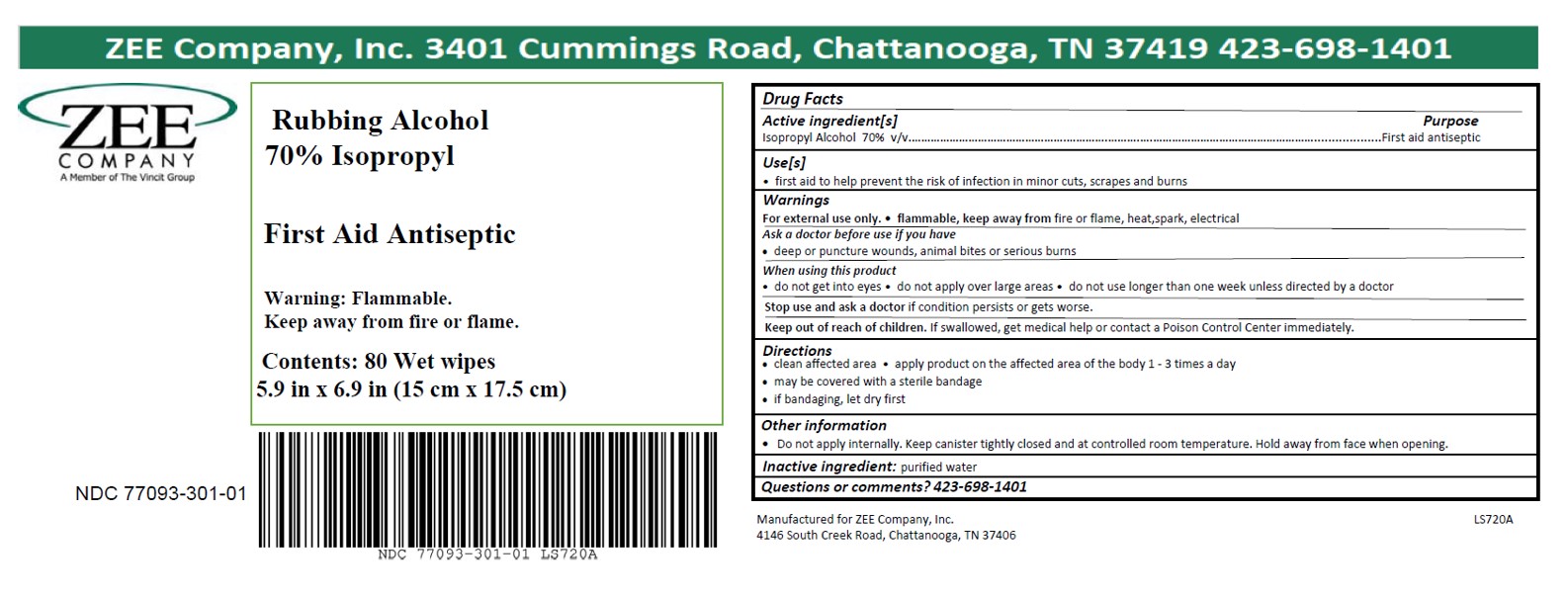 DRUG LABEL: Isopropyl Rubbing Alcohol Wipe
NDC: 77093-301 | Form: CLOTH
Manufacturer: Vincit Zee
Category: otc | Type: HUMAN OTC DRUG LABEL
Date: 20200710

ACTIVE INGREDIENTS: ISOPROPYL ALCOHOL 0.7 mL/1 mL
INACTIVE INGREDIENTS: WATER

Wipes - Rubbing Alcohol 70% Isopropyl

ACTIVE INGREDIENT

Isopropyl Alcohol 70% v/v

PURPOSE

First aid antiseptic

INDICATIONS AND USAGE

- first aid to help prevent the risk of infection in minor cuts, scrapes and burns

Ask a doctor before use if you have

- deep or puncture wounds, animal bites or serious burns

WARNINGS

- For external use only
- flammable, keep away from heat or flame

Stop use and ask a doctor if condition persists or gets worse

WHEN USING

- do not get into eyes
- do not apply over large areas of the body
- do not use longer than one week unless directed by a doctor

Keep out of reach of children. If swallowed, get medical help or contact a Poison Control Center immediately.

DOSAGE AND ADMINISTRATION

- clean affected area
- apply small amount of this product on the area 1-3 times daily
- if bandaging, let dry first
- may be covered with a sterile bandage

STORAGE AND HANDLING

Do not apply internally. Keeper canister tightly closed and at controlled room temperature. Hold away from face when opening.

INACTIVE INGREDIENT

purified water

PACKAGE LABEL

80 wet wipes NDC: 77093-301-01